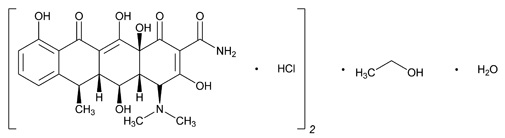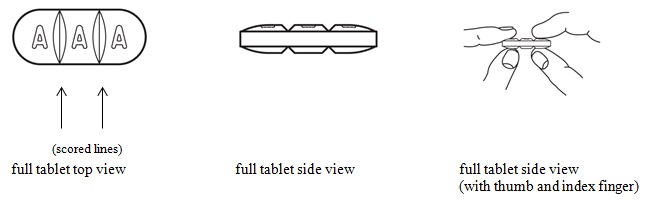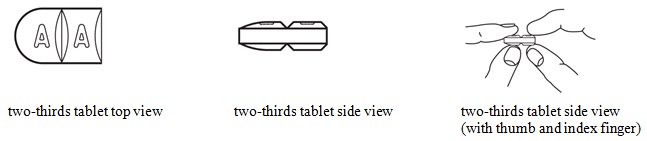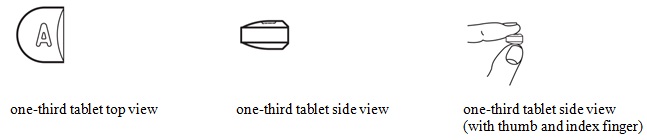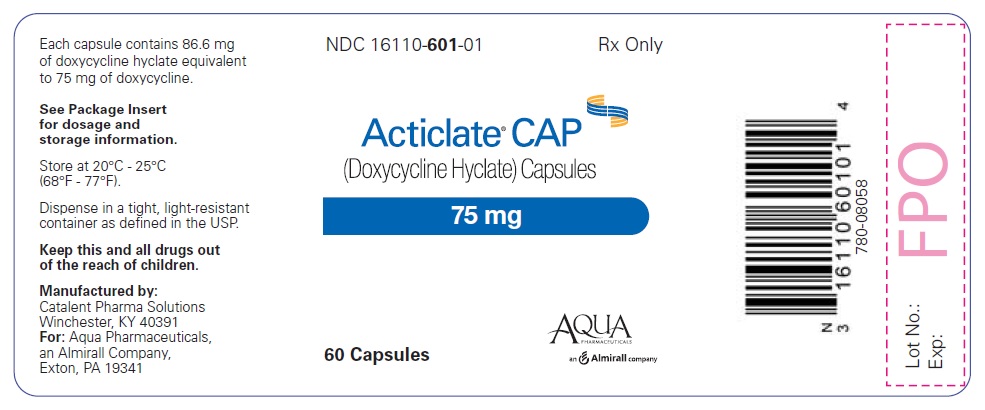 DRUG LABEL: Acticlate
NDC: 16110-601 | Form: CAPSULE
Manufacturer: Aqua Pharmaceuticals
Category: prescription | Type: HUMAN PRESCRIPTION DRUG LABEL
Date: 20171128

ACTIVE INGREDIENTS: DOXYCYCLINE HYCLATE 75 mg/1 1
INACTIVE INGREDIENTS: CELLULOSE, MICROCRYSTALLINE; MAGNESIUM STEARATE; TITANIUM DIOXIDE ; FD&C RED NO. 40; FD&C BLUE NO. 1

HIGHLIGHTS OF PRESCRIBING INFORMATION

These highlights do not include all the information needed to use ACTICLATE® and ACTICLATE® CAP safely and effectively. See full prescribing information for ACTICLATE® and ACTICLATE® CAP.
ACTICLATE® (doxycycline hyclate) tablets, for oral use
ACTICLATE® CAP (doxycycline hyclate) capsules, for oral use
Initial U.S. Approval: 1967

1 INDICATIONS AND USAGE

ACTICLATE® and ACTICLATE® CAP are tetracycline class drugs indicated for:

- Rickettsial infections (1.1)
- Sexually transmitted infections (1.2)
- Respiratory tract infections (1.3)
- Specific bacterial infections (1.4)
- Ophthalmic infections (1.5)
- Anthrax, including inhalational anthrax (post-exposure) (1.6)
- Alternative treatment for selected infections when penicillin is contraindicated (1.7)
- Adjunctive therapy for acute intestinal amebiasis and severe acne (1.8)
- Prophylaxis of malaria (1.9)

To reduce the development of drug-resistant bacteria and maintain the effectiveness of ACTICLATE and ACTICLATE CAP and other antibacterial drugs, ACTICLATE and ACTICLATE CAP should be used only to treat or prevent infections that are proven or strongly suspected to be caused by bacteria. (1.10)

2 DOSAGE AND ADMINISTRATION

- Important Administration Instructions for ACTICLATE and ACTICLATE CAP
  - ACTICLATE Tablets (150 mg) can be broken into two-thirds or one-third to provide a 50 mg and 100 mg strength, respectively. (2.1)
  - Swallow ACTICLATE CAP Capsule whole. Do not break, open, crush, dissolve or chew the capsule. (2.1)
- Dosage in Adults for ACTICLATE or ACTICLATE CAP:
  - The usual dosage is 200 mg on the first day of treatment (administered 100 mg every 12 hours) followed by a maintenance dose of 100 mg daily. (2.1)
  - In the management of more severe infections (particularly chronic infections of the urinary tract), 100 mg every 12 hours is recommended. (2.1)
- Dosage in Pediatric Patients for ACTICLATE or ACTICLATE CAP:
  - For all pediatric patients weighing less than 45 kg with severe or life-threatening infections (e.g., anthrax, Rocky Mountain spotted fever), the recommended dose is 2.2 mg per kg of body weight administered every 12 hours. Pediatric patients weighing 45 kg or more should receive the adult dose. (2.3)
  - For pediatric patients with less severe disease (greater than 8 years of age and weighing less than 45 kg), the recommended dose is 4.4 mg per kg of body weight divided into two doses on the first day of treatment, followed by a maintenance dose of 2.2 mg per kg of body weight (given as a single daily dose or divided into two doses. For pediatric patients weighing over 45 kg, the usual adult dose should be used. (2.3)
- See Full Prescribing Information for additional indication specific dosage information and important administration instructions for ACTICLATE and ACTICLATE CAP. (2.1, 2.4, 2.5)

3 DOSAGE FORMS AND STRENGTHS

- ACTICLATE Tablets: 75 mg and 150 mg (functionally scored) (3)
- ACTICLATE CAP Capsules: 75 mg (3)

4 CONTRAINDICATIONS

ACTICLATE and ACTICLATE CAP are contraindicated in persons who have shown hypersensitivity to any of the tetracyclines. (4)

5 WARNINGS AND PRECAUTIONS

- The use of drugs of the tetracycline-class during tooth development (last half of pregnancy, infancy and childhood to the age of 8 years) may cause permanent discoloration of the teeth (yellow-gray-brown). (2.2, 5.1)
- Clostridium difficile-associated diarrhea (CDAD) has been reported. Evaluate patients if diarrhea occurs. (5.2)
- Photosensitivity manifested by an exaggerated sunburn reaction has been observed in some individuals taking tetracyclines. Limit sun exposure. (5.3)
- Overgrowth of non-susceptible organisms, including fungi, may occur. If such infections occur, discontinue use and institute appropriate therapy. (5.4)

6 ADVERSE REACTIONS

Adverse reactions observed in patients receiving tetracyclines include anorexia, nausea, vomiting, diarrhea, rash, photosensitivity, urticaria, and hemolytic anemia. (6)

To report SUSPECTED ADVERSE REACTIONS, contact Aqua Pharmaceuticals at 1-866-665-2782, or FDA at 1-800-FDA-1088 or www.fda.gov/medwatch.

7 DRUG INTERACTIONS

- Patients who are on anticoagulant therapy may require downward adjustment of their anticoagulant dosage. (7.1)
- Avoid co-administration of tetracyclines with penicillin. (7.2)
- Absorption of tetracyclines, including ACTICLATE and ACTICLATE CAP is impaired by antacids containing aluminum, calcium, or magnesium, bismuth subsalicylate and iron-containing preparations. (7.3)
- Concurrent use of tetracyclines, including ACTICLATE and ACTICLATE CAP may render oral contraceptives less effective. (7.4)
- Barbiturates, carbamazepine and phenytoin decrease the half-life of doxycycline. (7.5)

8 USE IN SPECIFIC POPULATIONS

- Tetracycline-class drugs can cause fetal harm when administered to a pregnant woman, but data for doxycycline are limited. (5.6, 8.1)
- Tetracyclines are excreted in human milk; however, the extent of absorption of doxycycline in the breastfed infant is not known. ACTICLATE and ACTICLATE CAP use during nursing should be avoided if possible. (8.3)

FULL PRESCRIBING INFORMATION

1 INDICATIONS AND USAGE

1.1 Rickettsial Infections

ACTICLATE® and ACTICLATE® CAP are indicated for treatment of Rocky Mountain spotted fever, typhus fever and the typhus group, Q fever, rickettsial pox, and tick fevers caused by Rickettsiae.

1.2 Sexually Transmitted Infections

ACTICLATE and ACTICLATE CAP are indicated for treatment of the following sexually transmitted infections:

- Uncomplicated urethral, endocervical or rectal infections caused by Chlamydia trachomatis.
- Nongonococcal urethritis caused by Ureaplasma urealyticum.
- Lymphogranuloma venereum caused by Chlamydia trachomatis.
- Granuloma inguinale caused by Klebsiella granulomatis.
- Uncomplicated gonorrhea caused by Neisseria gonorrhoeae.
- Chancroid caused by Haemophilus ducreyi.

1.3 Respiratory Tract Infections

ACTICLATE and ACTICLATE CAP are indicated for treatment of the following respiratory tract infections:

- Respiratory tract infections caused by Mycoplasma pneumoniae.
- Psittacosis (ornithosis) caused by Chlamydophila psittaci.
- Because many strains of the following groups of microorganisms have been shown to be resistant to doxycycline, culture and susceptibility testing are recommended.
- Doxycycline is indicated for treatment of infections caused by the following microorganisms, when bacteriological testing indicates appropriate susceptibility to the drug:
- Respiratory tract infections caused by Haemophilus influenzae.
- Respiratory tract infections caused by Klebsiella species.
- Upper respiratory infections caused by Streptococcus pneumoniae.

1.4 Specific Bacterial Infections

ACTICLATE and ACTICLATE CAP are indicated for treatment of the following specific bacterial infections:

- Relapsing fever due to Borrelia recurrentis.
- Plague due to Yersinia pestis.
- Tularemia due to Francisella tularensis.
- Cholera caused by Vibrio cholerae.
- Campylobacter fetus infections caused by Campylobacter fetus.
- Brucellosis due to Brucella species (in conjunction with streptomycin).
- Bartonellosis due to Bartonella bacilliformis.

Because many strains of the following groups of microorganisms have been shown to be resistant to doxycycline, culture and susceptibility testing are recommended.

ACTICLATE and ACTICLATE CAP are indicated for treatment of infections caused by the following gram-negative microorganisms, when bacteriological testing indicates appropriate susceptibility to the drug:

- Escherichia coli
- Enterobacter aerogenes
- Shigella species
- Acinetobacter species
- Urinary tract infections caused by Klebsiella species.

1.5 Ophthalmic Infections

ACTICLATE and ACTICLATE CAP are indicated for treatment of the following ophthalmic infections:

- Trachoma caused by Chlamydia trachomatis, although the infectious agent is not always eliminated as judged by immunofluorescence.
- Inclusion conjunctivitis caused by Chlamydia trachomatis.

1.6 Anthrax Including Inhalational Anthrax (Post-Exposure)

ACTICLATE and ACTICLATE CAP are indicated for the treatment of Anthrax due to Bacillus anthracis, including inhalational anthrax (post-exposure); to reduce the incidence or progression of disease following exposure to aerosolized Bacillus anthracis.

1.7 Alternative Treatment for Selected Infections when Penicillin is Contraindicated

ACTICLATE and ACTICLATE CAP are indicted as an alternative treatment for the following selected infections when penicillin is contraindicated:

- Syphilis caused by Treponema pallidum.
- Yaws caused by Treponema pallidum subspecies pertenue.
- Listeriosis due to Listeria monocytogenes.
- Vincent’s infection caused by Fusobacterium fusiforme.
- Actinomycosis caused by Actinomyces israelii.
- Infections caused by Clostridium species.

1.8 Adjunctive Therapy for Acute Intestinal Amebiasis and Severe Acne

In acute intestinal amebiasis, ACTICLATE and ACTICLATE CAP may be a useful adjunct to amebicides.

In severe acne, ACTICLATE and ACTICLATE CAP may be useful adjunctive therapy.

1.9 Prophylaxis of Malaria

ACTICLATE and ACTICLATE CAP are indicated for the prophylaxis of malaria due to Plasmodium falciparum in short-term travelers (less than 4 months) to areas with chloroquine and/or pyrimethamine-sulfadoxine resistant strains [see Dosage and Administration (2.4) and Patient Counseling Information (17)].

1.10 Usage

To reduce the development of drug-resistant bacteria and maintain the effectiveness of ACTICLATE and ACTICLATE CAP and other antibacterial drugs, ACTICLATE and ACTICLATE CAP should be used only to treat or prevent infections that are proven or strongly suspected to be caused by susceptible bacteria. When culture and susceptibility information are available, they should be considered in selecting or modifying antibacterial therapy. In the absence of such data, local epidemiology and susceptibility patterns may contribute to the empiric selection of therapy.

2 DOSAGE AND ADMINISTRATION

2.1 Important Administration Instructions

- The usual dosage and frequency of administration of ACTICLATE and ACTICLATE CAP differs from that of the other tetracyclines. Exceeding the recommended dosage may result in an increased incidence of adverse reactions.
- Administer ACTICLATE and ACTICLATE CAP with adequate amounts of fluid to wash down the drugs and reduce the risk of esophageal irritation and ulceration [see Adverse Reactions (6)].
- If gastric irritation occurs, ACTICLATE and ACTICLATE CAP may be given with food or milk [see Clinical Pharmacology (12.3)]
- Swallow ACTICLATE CAP whole. Do not break, open, crush, dissolve or chew the capsule.
- ACTICLATE tablets (150 mg) can be broken into two-thirds or one-third to provide a 100 mg and 50 mg strength, respectively [see FDA-approved patient labeling].

2.2 Dosage in Adult Patients

- The usual dosage of ACTICLATE is 200 mg on the first day of treatment (administered 100 mg every 12 hours) followed by a maintenance dose of 100 mg daily. The maintenance dose may be administered as a single dose or as 50 mg every 12 hours.
- In the management of more severe infections (particularly chronic infections of the urinary tract), 100 mg every 12 hours is recommended.
- For certain selected specific indications, the recommended duration or dosage and duration of ACTICLATE or ACTICLATE CAP in adult patients are as follows:
  1. Streptococcal infections, therapy should be continued for 10 days.
  2. Uncomplicated urethral, endocervical, or rectal infection caused by Chlamydia trachomatis: 100 mg by mouth twice-a-day for 7 days.
  3. Uncomplicated gonococcal infections in adults (except anorectal infections in men): 100 mg, by mouth, twice-a-day for 7 days. As an alternate single visit dose, administer 300 mg stat followed in one hour by a second 300 mg dose.
  4. Nongonococcal urethritis (NGU) caused by C. trachomatis and U. urealyticum: 100 mg by mouth twice-a-day for 7 days.
  5. Syphilis – early: Patients who are allergic to penicillin should be treated with doxycycline 100 mg by mouth twice-a-day for 2 weeks.
  6. Syphilis of more than one year’s duration: Patients who are allergic to penicillin should be treated with doxycycline 100 mg by mouth twice-a-day for 4 weeks.
  7. Acute epididymo-orchitis caused by N. gonorrhoeae: 100 mg by mouth, twice-a-day for at least 10 days.
  8. Acute epididymo-orchitis caused by C. trachomatis: 100 mg, by mouth, twice-a-day for at least 10 days.

2.3 Dosage in Pediatric Patients

- For all pediatric patients weighing less than 45 kg with severe or life threatening infections (e.g., anthrax, Rocky Mountain spotted fever), the recommended dosage of ACTICLATE and ACTICLATE CAP is 2.2 mg per kg of body weight administered every 12 hours. Pediatric patients weighing 45 kg or more should receive the adult dose [see Warnings and Precautions (5.1)].
- For pediatric patients with less severe disease (greater than 8 years of age and weighing less than 45 kg), the recommended dosage schedule of ACTICLATE and ACTICLATE CAP is 4.4 mg per kg of body weight divided into two doses on the first day of treatment, followed by a maintenance dose of 2.2 mg per kg of body weight (given as a single daily dose or divided into twice daily doses). For pediatric patients weighing over 45 kg, the usual adult dose should be used.

2.4 Dosage for Prophylaxis of Malaria

For adults, the recommended dose of ACTICLATE is 100 mg daily.

For pediatric patients 8 years of age and older, the recommended dosage of ACTICLATE and ACTICLATE CAP is 2 mg per kg of body weight administered once daily. Pediatric patients weighing 45 kg or more should receive the adult dose.

Prophylaxis should begin 1 or 2 days before travel to the malarious area. Prophylaxis should be continued daily during travel in the malarious area and for 4 weeks after the traveler leaves the malarious area.

2.5 Dosage for Inhalational Anthrax (Post-Exposure)

For adults, the recommended dosage is 100 mg, of ACTICLATE, by mouth, twice-a-day for 60 days.

For pediatric patients weighing less than 45 kg, the recommended dosage of ACTICLATE and ACTICLATE CAP is 2.2 mg per kg of body weight, by mouth, twice-a-day for 60 days. Pediatric patients weighing 45 kg or more should receive the adult dose.

3 DOSAGE FORMS AND STRENGTHS

ACTICLATE Tablets:

ACTICLATE (doxycycline hyclate) Tablets, 75 mg are round, convex, light-teal, film-coated, tablets with “75” debossed on one side of the tablet and “AQ101” debossed on the other (each tablet contains 75 mg doxycycline as 86.6 mg doxycycline hyclate).

ACTICLATE (doxycycline hyclate) Tablets, 150 mg are oval-shaped, convex, mossy-green, film-coated tablets. Each side of the functionally scored tablet has two parallel score lines for splitting into 3 equal portions with “A” debossed on each portion of one side of the tablet, and no debossing on the other (each tablet contains 150 mg doxycycline as 173.2 mg doxycycline hyclate).

ACTICLATE CAP Capsules:

ACTICLATE CAP (doxycycline hyclate) Capsules, 75 mg have a navy blue opaque body and cap with the inscription “AQUA 101C75” in black (each capsule contains 75 mg doxycycline as 86.6 mg doxycycline hyclate).

4 CONTRAINDICATIONS

ACTICLATE and ACTICLATE CAP are contraindicated in persons who have shown hypersensitivity to any of the tetracyclines.

5 WARNINGS AND PRECAUTIONS

5.1 Tooth Development

The use of drugs of the tetracycline-class during tooth development (last half of pregnancy, infancy and childhood to the age of 8 years) may cause permanent discoloration of the teeth (yellow-gray-brown). This adverse reaction is more common during long-term use of the drugs but it has been observed following repeated short-term courses. Enamel hypoplasia has also been reported. Use ACTICLATE and ACTICLATE CAP in pediatric patients 8 years of age or less only when the potential benefits are expected to outweigh the risks in severe or life-threatening conditions (e.g., anthrax, Rocky Mountain spotted fever), particularly when there are no alternative therapies.

5.2 Clostridium difficile Associated Diarrhea

Clostridium difficile associated diarrhea (CDAD) has been reported with use of nearly all antibacterial agents, including ACTICLATE and ACTICLATE CAP, and may range in severity from mild diarrhea to fatal colitis. Treatment with antibacterial agents alters the normal flora of the colon leading to overgrowth of C. difficile.

C. difficile produces toxins A and B which contribute to the development of CDAD. Hypertoxin producing strains of C. difficile cause increased morbidity and mortality, as these infections can be refractory to antibacterial therapy and may require colectomy. CDAD must be considered in all patients who present with diarrhea following antibacterial use. Careful medical history is necessary since CDAD has been reported to occur over two months after the administration of antibacterial agents.

If CDAD is suspected or confirmed, ongoing antibacterial use not directed against C. difficile may need to be discontinued. Appropriate fluid and electrolyte management, protein supplementation, antibacterial treatment of C. difficile, and surgical evaluation should be instituted as clinically indicated.

5.3 Photosensitivity

Photosensitivity manifested by an exaggerated sunburn reaction has been observed in some individuals taking tetracyclines. Patients apt to be exposed to direct sunlight or ultraviolet light should be advised that this reaction can occur with tetracycline drugs, and treatment should be discontinued at the first evidence of skin erythema.

5.4 Potential for Microbial Overgrowth

ACTICLATE and ACTICLATE CAP may result in overgrowth of non-susceptible organisms, including fungi. If such infections occur, discontinue use and institute appropriate therapy.

5.5 Severe Skin Reactions

Severe skin reactions, such as exfoliative dermatitis, erythema multiforme, Stevens-Johnson syndrome, toxic epidermal necrolysis, and drug reaction with eosinophilia and systemic symptoms (DRESS) have been reported in patients receiving doxycycline [See Adverse Reactions (6)]. If severe skin reactions occur, doxycycline should be discontinued immediately and appropriate therapy should be instituted.

5.6 Intracranial Hypertension

Intracranial hypertension (IH, pseudotumor cerebri) has been associated with the use of tetracyclines including ACTICLATE and ACTICLATE CAP. Clinical manifestations of IH include headache, blurred vision, diplopia, and vision loss; papilledema can be found on fundoscopy. Women of childbearing age who are overweight or have a history of IH are at greater risk for developing tetracycline associated IH. Concomitant use of isotretinoin and ACTICLATE and ACTICLATE CAP should be avoided because isotretinoin is also known to cause pseudotumor cerebri.

Although IH typically resolves after discontinuation of treatment, the possibility for permanent visual loss exists. If visual disturbance occurs during treatment, prompt ophthalmologic evaluation is warranted. Since intracranial pressure can remain elevated for weeks after drug cessation patients should be monitored until they stabilize.

5.7 Delayed Skeletal Development

All tetracyclines form a stable calcium complex in any bone-forming tissue. A decrease in fibula growth rate has been observed in prematures given oral tetracycline in doses of 25 mg per kg every six hours. This reaction was shown to be reversible when the drug was discontinued.

Results of animal studies indicate that tetracyclines cross the placenta, are found in fetal tissues, and can have toxic effects on the developing fetus (often related to retardation of skeletal development). Evidence of embryotoxicity also has been noted in animals treated early in pregnancy. Tetracycline-class drugs can cause fetal harm when administered to a pregnant woman, but data for doxycycline are limited. If any tetracycline is used during pregnancy or if the patient becomes pregnant while taking these drugs, the patient should be apprised of the potential hazard to the fetus.

5.8 Antianabolic Action

The antianabolic action of the tetracyclines may cause an increase in BUN. Studies to date indicate that this does not occur with the use of doxycycline in patients with impaired renal function.

5.9 Incomplete Suppression of Malaria

Doxycycline offers substantial but not complete suppression of the asexual blood stages of Plasmodium strains.

Doxycycline does not suppress P. falciparum’s sexual blood stage gametocytes. Subjects completing this prophylactic regimen may still transmit the infection to mosquitoes outside endemic areas.

5.10 Development of Drug-Resistant Bacteria

Prescribing ACTICLATE and ACTICLATE CAP in the absence of a proven or strongly suspected bacterial infection or a prophylactic indication is unlikely to provide benefit to the patient and increases the risk of the development of drug-resistant bacteria.

5.11 Laboratory Monitoring for Long-Term Therapy

In long-term therapy, periodic laboratory evaluation of organ systems, including hematopoietic, renal and hepatic studies should be performed.

6 ADVERSE REACTIONS

The following adverse reactions have been identified during clinical trials or post-approval use of tetracycline-class drugs, including doxycycline. Because these reactions are reported voluntarily from a population of uncertain size, it is not always possible to reliably estimate their frequency or establish a causal relationship to drug exposure.

Gastrointestinal: Anorexia, nausea, vomiting, diarrhea, glossitis, dysphagia, enterocolitis, and inflammatory lesions (with monilial overgrowth) in the anogenital region, and pancreatitis. Hepatotoxicity has been reported. These reactions have been caused by both the oral and parenteral administration of tetracyclines. Superficial discoloration of the adult permanent dentition, reversible upon drug discontinuation and professional dental cleaning has been reported. Permanent tooth discoloration and enamel hypoplasia may occur with drugs of the tetracycline class when used during tooth development [See Warnings and Precautions (5.1)]. Instances of esophagitis and esophageal ulcerations have been reported in patients receiving capsule and tablet forms of drugs in the tetracycline-class. Most of these patients took medications immediately before going to bed [see Dosage and Administration (2.1)].

Skin: Maculopapular and erythematous rashes, Stevens-Johnson syndrome, toxic epidermal necrolysis, exfoliative dermatitis, and erythema multiforme have been reported. Photosensitivity has been reported [see Warnings and Precautions (5.3)].

Renal: Rise in BUN has been reported and is apparently dose-related [see Warnings and Precautions (5.8)].

Hypersensitivity reactions: Urticaria, angioneurotic edema, anaphylaxis, anaphylactoid purpura, serum sickness, pericarditis, and exacerbation of systemic lupus erythematosus, and drug reaction with eosinophilia and systemic symptoms (DRESS).

Blood: Hemolytic anemia, thrombocytopenia, neutropenia, and eosinophilia have been reported.

Intracranial Hypertension: Intracranial hypertension (IH, pseudotumor cerebri) has been associated with the use of tetracyclines [see Warnings and Precautions (5.6)].

Thyroid Gland Changes: When given over prolonged periods, tetracyclines have been reported to produce brown-black microscopic discoloration of thyroid glands. No abnormalities of thyroid function are known to occur.

7 DRUG INTERACTIONS

7.1 Anticoagulant Drugs

Because tetracyclines have been shown to depress plasma prothrombin activity, patients who are on anticoagulant therapy may require downward adjustment of their anticoagulant dosage.

7.2 Penicillin

Since bacteriostatic drugs may interfere with the bactericidal action of penicillin, it is advisable to avoid giving tetracyclines, including ACTICLATE and ACTICLATE CAP in conjunction with penicillin.

7.3 Antacids and Iron Preparations

Absorption of tetracyclines, including ACTICLATE and ACTICLATE CAP is impaired by antacids containing aluminum, calcium, or magnesium, bismuth subsalicylate, and iron-containing preparations.

7.4 Oral Contraceptives

Concurrent use of tetracyclines, including ACTICLATE and ACTICLATE CAP may render oral contraceptives less effective.

7.5 Barbiturates and Anti-Epileptics

Barbiturates, carbamazepine, and phenytoin decrease the half-life of doxycycline.

7.6 Penthrane®

The concurrent use of tetracycline and Penthrane® (methoxyflurane) has been reported to result in fatal renal toxicity.

7.7 Drug and Laboratory Test Interactions

False elevations of urinary catecholamines may occur due to interference with the fluorescence test.

8 USE IN SPECIFIC POPULATIONS

8.1 Pregnancy

TERATOGENIC EFFECTS

Teratogenic Effects. Pregnancy Category D: [see Warnings and Precautions (5.7)]
There are no adequate and well-controlled studies on the use of doxycycline in pregnant women. The vast majority of reported experience with doxycycline during human pregnancy is short-term, first trimester exposure. There are no human data available to assess the effects of long-term therapy of doxycycline in pregnant women such as that proposed for the treatment of anthrax exposure. An expert review of published data on experiences with doxycycline use during pregnancy by TERIS - the Teratogen Information System - concluded that therapeutic doses during pregnancy are unlikely to pose a substantial teratogenic risk (the quantity and quality of data were assessed as limited to fair), but the data are insufficient to state that there is no risk.^1

A case-control study (18,515 mothers of infants with congenital anomalies and 32,804 mothers of infants with no congenital anomalies) shows a weak but marginally statistically significant association with total malformations and use of doxycycline anytime during pregnancy. Sixty-three (0.19%) of the controls and 56 (0.30%) of the cases were treated with doxycycline. This association was not seen when the analysis was confined to maternal treatment during the period of organogenesis (that is, in the second and third months of gestation), with the exception of a marginal relationship with neural tube defect based on only two-exposed cases.^2

A small prospective study of 81 pregnancies describes 43 pregnant women treated for 10 days with doxycycline during early first trimester. All mothers reported their exposed infants were normal at 1 year of age.^3

Nonteratogenic effects: [see Warnings and Precautions (5.1, 5.7)].

8.3 Nursing Mothers

Tetracyclines are excreted in human milk, however, the extent of absorption of tetracyclines including doxycycline, by the breastfed infant is not known. Short-term use by lactating women is not necessarily contraindicated. The effects of prolonged exposure to doxycycline in breast milk are unknown^4. Because of the potential for serious adverse reactions in nursing infants from doxycycline, a decision should be made whether to discontinue nursing or to discontinue the drug, taking into account the importance of the drug to the mother [see Warnings and Precautions (5.1, 5.7)].

8.4 Pediatric Use

Because of the effects of drugs of the tetracycline-class on tooth development and growth, use ACTICLATE and ACTICLATE CAP in pediatric patients 8 years of age or less only when the potential benefits are expected to outweigh the risks in severe or life-threatening conditions (e.g., anthrax, Rocky Mountain spotted fever), particularly when there are no alternative therapies [see Warnings and Precautions (5.1, 5.7) and Dosage and Administration (2.1, 2.5)].

8.5 Geriatric Use

Clinical studies of doxycycline hyclate tablets did not include sufficient numbers of subjects aged 65 and over to determine whether they respond differently from younger subjects. Other reported clinical experience has not identified differences in responses between the elderly and younger patients. ACTICLATE Tablets each contains less than 1 mg of sodium.

10 OVERDOSAGE

In case of overdosage, discontinue medication, treat symptomatically and institute supportive measures. Dialysis does not alter serum half-life and thus would not be of benefit in treating cases of overdosage.

11 DESCRIPTION

ACTICLATE (doxycycline hyclate) Tablets and ACTICLATE CAP (doxycycline hyclate) Capsules contain doxycycline hyclate, a tetracycline class drug synthetically derived from oxytetracycline, in an immediate release formulation for oral administration.

The molecular formula of doxycycline hyclate is (C22H24N2O8 • HCl)2• C2H6O• H2O and the molecular weight of doxycycline hyclate is 1025.87. The chemical name for doxycycline hyclate is:
4-(Dimethylamino)-1,4,4a,5,5a,6,11,12a-octahydro-3,5,10,12,12a-pentahydroxy-6-methyl-1,11-dioxo-2-naphthacenecarboxamide monohydrochloride, compound with ethyl alcohol (2:1), monohydrate.

The structural formula for doxycycline hyclate is:

Figure 1: Structure of Doxycycline Hyclate

Doxycycline hyclate is a yellow crystalline powder soluble in water and in solutions of alkali hydroxides and carbonates.

ACTICLATE Tablet:
ACTICLATE is available as 75 mg and 150 mg tablets. Each 75 mg tablet contains 86.6 mg of doxycycline hyclate equivalent to 75 mg of doxycycline. Each 150 mg tablet contains 173.2 mg of doxycycline hyclate equivalent to 150 mg of doxycycline.
Inactive ingredients in the tablet formulation are: microcrystalline cellulose, sodium lauryl sulfate, croscarmellose sodium and magnesium stearate. Film-coating contains: polyvinyl alcohol, titanium dioxide, polyethylene glycol, talc, FD&C Blue #1 (75 mg Tablet), FD&C Blue #2 (150 mg Tablet) and yellow iron oxide (150 mg Tablet). ACTICLATE Tablets, 75 mg contain 0.34 mg (0.0146 mEq) of sodium. ACTICLATE Tablets, 150 mg contain 0.68 mg (0.0295 mEq) of sodium.

ACTICLATE CAP Capsule:
ACTICLATE CAP is available as 75 mg capsules. Each 75 mg capsule contains 86.6 mg of doxycycline hyclate equivalent to 75 mg of doxycycline.

Inactive ingredients in the capsule formulation are: microcrystalline cellulose, magnesium stearate, and a hard gelatin capsule which contains titanium dioxide, FD&C Red #40 and FD&C Blue #1. The capsules are printed with edible ink containing ammonium hydroxide, propylene glycol, isopropyl alcohol, N-butyl alcohol, black iron oxide, and shellac glaze in ethanol.

12 CLINICAL PHARMACOLOGY

12.1 Mechanism of Action

Doxycycline is a tetracycline-class antimicrobial drug [see Microbiology (12.4)].

12.3 Pharmacokinetics

Absorption
ACTICLATE (doxycycline hyclate) Tablets: Following administration of a single 300 mg dose to adult volunteers, average peak plasma doxycycline levels were 3.0 mcg per mL at 3 hours, decreasing to 1.18 mcg per mL at 24 hours. The mean Cmax and AUC0-∞ of doxycycline are 24% and 15% lower, respectively, following single dose administration of ACTICLATE, 150 mg tablets with a high fat meal (including milk) compared to fasted conditions. The clinical significance of these decreases is unknown.
ACTICLATE CAP (doxycycline hyclate) Capsules. Following administration of a single 300 mg dose to adult volunteers, average peak plasma doxycycline levels were 2.8 mcg per mL at 3 hours, decreasing to 1.1 mcg per mL at 24 hours. The mean Cmax of doxycycline is approximately 20% lower and the AUC0-∞ is unchanged following single dose administration of ACTICLATE CAP Capsules with a high fat meal (including milk) compared to fasted conditions. The clinical significance of this decrease in Cmax is unknown.

Excretion
Tetracyclines are concentrated in bile by the liver and excreted in the urine and feces at high concentrations and in a biologically active form.

Excretion of doxycycline by the kidney is about 40% per 72 hours in individuals with a creatinine clearance of about 75 mL per minute. This percentage may fall as low as 1% per 72 hours to 5% per 72 hours in individuals with a creatinine clearance below 10 mL per minute. Studies have shown no significant difference in the serum half-life of doxycycline (range 18 to 22 hours) in individuals with normal and severely impaired renal function. Hemodialysis does not alter the serum half-life.

12.4 Microbiology

Mechanism of Action
Doxycycline inhibits bacterial protein synthesis by binding to the 30S ribosomal subunit. Doxycycline has bacteriostatic activity against a broad range of Gram-positive and Gram-negative bacteria.
Resistance
Cross resistance with other tetracyclines is common.
Antimicrobial Activity
Doxycycline has been shown to be active against most isolates of the following microorganisms, both in vitro and in clinical infections [see Indications and Usage (1)].

Gram-negative bacteria
Acinetobacter species
Bartonella bacilliformis
Brucella species
Campylobacter fetus
Enterobacter aerogenes
Escherichia coli
Francisella tularensis
Haemophilus ducreyi
Haemophilus influenzae
Klebsiella granulomatis
Klebsiella species
Neisseria gonorrhoeae
Shigella species
Vibrio cholerae
Yersinia pestis

Gram-positive bacteria
Bacillus anthracis
Listeria monocytogenes
Streptococcus pneumoniae

Anaerobic bacteria
Clostridium species
Fusobacterium fusiforme
Propionibacterium acnes

Other bacteria
Nocardiae and other aerobic Actinomyces species
Borrelia recurrentis
Chlamydophila psittaci
Chlamydia trachomatis
Mycoplasma pneumoniae
Rickettsiae species
Treponema pallidum
Treponema pallidum subspecies pertenue
Ureaplasma urealyticum

Parasites
Balantidium coli
Entamoeba species
Plasmodium falciparum*
*Doxycycline has been found to be active against the asexual erythrocytic forms of Plasmodium falciparum, but not against the gametocytes of P. falciparum. The precise mechanism of action of the drug is not known.

Susceptibility Testing Methods
When available, the clinical microbiology laboratory should provide cumulative reports of in vitro susceptibility test results for antimicrobial drugs used in local hospitals and practice as periodic reports that describe the susceptibility profile of nosocomial and community-acquired pathogens. These reports should aid in the selection of an appropriate antibacterial drug for treatment.

Dilution techniques:
Quantitative methods are used to determine antimicrobial minimum inhibitory concentrations (MICs). These MICs provide estimates of the susceptibility of bacteria to antimicrobial compounds. The MICs values should be determined using a standardized test method^5,6,7,8,9 (broth and/or agar). The MIC values should be interpreted according to criteria provided in Table 1.

Diffusion techniques:
Quantitative methods that require measurement of zone diameters can also provide reproducible estimates of the susceptibility of bacteria to antimicrobial compounds.

The zone size should be determined using a standardized test method^5,7,10. This procedure uses paper disks impregnated with 30 mcg doxycycline to test the susceptibility of bacteria to doxycycline. The disk diffusion interpretive criteria are provided in Table 1.

Anaerobic Techniques:
For anaerobic bacteria, the susceptibility to doxycycline can be determined by a standardized test method^5,11. The MIC values obtained should be interpreted according to the criteria provided in Table 1.

Table 1: Susceptibility Test Interpretive Criteria for Doxycycline and Tetracycline
Pathogena | Minimal Inhibitory Concentrations (mcg/mL) |  |  | Disk Diffusion Zone Diameters (mm) |  |  | Agar Dilution (mcg/mL)
Pathogena | S | I | R | S | I | R | S | I | R
Acinetobacter spp.
Doxycycline | ≤4 | 8 | ≥16 | ≥13 | 10 - 12 | ≤9 | - | - | -
Tetracycline | ≤4 | 8 | ≥16 | ≥15 | 12-14 | ≤11 | - | - | -
Anaerobes
Tetracycline | - | - | - | - | - | - | ≤4 | 8 | ≥16
Bacillus anthracisb
Doxycycline | ≤1 | - | - | - | - | - | - | - | -
Tetracycline | ≤1 | - | - | - | - | - | - | - | -
Brucella speciesb
Doxycycline | ≤1 | - | - | - | - | - | - | - | -
Tetracycline | ≤1 | - | - | - | - | - | - | - | -
Enterobacteriaceae
Doxycycline | ≤4 | 8 | ≥16 | ≥14 | 11-13 | ≤10 | - | - | -
Tetracycline | ≤4 | 8 | ≥16 | ≥15 | 12-14 | ≤11 | - | - | -
Franciscella tularensisc
Doxycycline | ≤4 | - | - | - | - | - | - | - | -
Tetracycline | ≤4 | - | - | - | - | - | - | - | -
Haemophilus influenzae
Tetracycline | ≤2 | 4 | ≥8 | ≥29 | 26-28 | ≤25 | - | - | -
Mycoplasma pneumoniaeb
Tetracycline |  | - | - | - | - | - | ≤2 | - | -
Nocardiae and other aerobic Actinomyces speciesb
Doxycycline | ≤1 | 2-4 | ≥8 | - | - | - |  | - | -
Neisseria gonorrhoeae speciesc
Tetracycline | - | - | - | ≥38 | 31-37 | ≤30 | ≤0.25 | 0.5-1 | ≥2
Streptococcus pneumoniae
Doxycycline | ≤0.25 | 0.5 | ≥1 | ≥28 | 25-27 | ≤24 | - | - | -
Tetracycline | ≤1 | 2 | ≥4 | ≥28 | 25-27 | ≤24 | - | - | -
Vibrio cholerae
Doxycycline | ≤4 | 8 | ≥16 | - | - | - | - | - | -
Tetracycline | ≤4 | 8 | ≥16 | - | - | - | - | - | -
Yersinia pestis
Doxycycline | ≤4 | 8 | ≥16 | - | - | - | - | - | -
Tetracycline | ≤4 | 8 | ≥16 | - | - | - | - | - | -
Ureaplasma urealyticum
Tetracycline | - | - | - | - | - | - | ≤1 | - | ≥2
a Organisms susceptible to tetracycline are also considered susceptible to doxycycline. However, some organisms that are intermediate or resistant to tetracycline may be susceptible to doxycycline.
b The current absence of resistance isolates precludes defining any results other than "Susceptible". If isolates yielding MIC results other than susceptible, they should be submitted to a reference laboratory for further testing.
c Gonococci with 30 mcg tetracycline disk zone diameters of less than 19 mm usually indicate a plasmid-mediated tetracycline resistant Neisseria gonorrhoeae isolate. Resistance in these strains should be confirmed by a dilution test (MIC ≥ 16 mcg per mL).

Doxycycline susceptibility testing interpretive criteria for anaerobes, Haemophilus influenzae, Mycoplasma pneumoniae, Neisseria gonorrhoeae, and Ureaplasma urealyticum have not been established. Isolates of these species that are susceptible to tetracycline are also considered susceptible to doxycycline.^5

A report of Susceptible (S) indicates that the antimicrobial drug is likely to inhibit growth of the pathogen if the antimicrobial drug reaches the concentration usually achievable at the site of infection. A report of Intermediate (I) indicates that the result should be considered equivocal, and, if the microorganism is not fully susceptible to alternative, clinically feasible drugs, the test should be repeated. This category implies possible clinical applicability in body sites where the drug product is physiologically concentrated or in situations where high dosage of drug can be used. This category also provides a buffer zone that prevents small uncontrolled technical factors from causing major discrepancies in interpretation. A report of Resistant (R) indicates that the antimicrobial drug is not likely to inhibit growth of the pathogen if the antimicrobial drug reaches the concentration usually achievable at the infection site; other therapy should be selected.

Quality Control
Standardized susceptibility test procedures require the use of laboratory controls to monitor and ensure the accuracy and precision of the supplies and reagents used in the assay, and the techniques of the individuals performing the test^5,6,7,8,9,10,11. Standard doxycycline powders should provide the following range of MIC values noted in Table 2. For the diffusion technique using the 30 mcg doxycycline disk, the criteria noted in Table 2 should be achieved.

Table 2: Acceptable Quality Control Ranges for Doxycycline and Tetracycline
QC Strain | Minimal Inhibitory Concentration (mcg per mL) | Disk Diffusion (zone diameter mm) | Agar Dilution (mcg/ml)
Enterococcus faecalis ATCCa 29212
Doxycycline | 2 – 8 | - | -
Tetracycline | 8-32 | - | -
Escherichia coli ATCC 25922
Doxycycline | 0.5 – 2 | 18 – 24 | -
Tetracycline | 0.5-2 | 18-25 | -
Eggerthella lenta ATCC 43055
Doxycycline | 2 – 16 | - | -
Haemophilus influenza ATCC 49247
Tetracycline | 4-32 | 14-22 | -
Neisseria gonorrhoeae ATCC 49226
Tetracycline | - | 30-42 | 0.25-1
Staphylococcus aureus ATCC 25923
Doxycycline | - | 23 – 29 | -
Tetracycline | - | 24-30 | -
Staphylococcus aureus ATCC 29213
Doxycycline | 0.12 - 0.5 | - | -
Tetracycline | 0.12-1 | - | -
Streptococcus pneumoniae ATCC 49619
Doxycycline | 0.016 - 0.12 | 25-34 | -
Tetracycline | 0.06-0.5 | 27-31 | -
Bacteroides frugilis ATCC 25285
Tetracycline | - | - | 0.125-0.5
Bacteroides thetaiotaomicron ATCC 29741
Doxycycline | 2 – 8 | - | -
Tetracycline | - | - | 8-32
Mycoplasma hominis ATCC 23114
Tetracycline | - | - | 0.12-1
Mycoplasma pneumoniae ATCC 29342
Tetracycline | 0.06-0.5 | - | 0.06-0.5
Ureaplasma urealyticum ATCC 33175
Tetracycline | - | - | ≥8
a ATCC is the American Type Culture Collection

13 NONCLINICAL TOXICOLOGY

13.1 Carcinogenesis, Mutagenesis, Impairment of Fertility

Long-term studies in animals to evaluate carcinogenic potential of ACTICLATE (doxycycline hyclate) and ACTICLATE CAP (doxycycline hyclate) have not been conducted.
However, a 2 year carcinogenicity study with doxycycline administered daily by oral gavage to adult rats (20, 75, 200 mg/kg/day) demonstrated an increase in uterine polyps in female rats at 200 mg/kg/day (10 times the maximum recommended daily adult dose of ACTICLATE and ACTICLATE CAP based on body surface area comparison) with no change in tumor incidence in male rats at the same dose. A 2-year carcinogenicity study with doxycycline administered daily by oral gavage to adult male (maximum dose 150 mg/kg/day) and female (maximum dose 300 mg/kg/day) mice showed no changes in tumor incidence, at approximately 4 and 7 times the maximum recommended daily adult dose of ACTICLATE and ACTICLATE CAP, based on a body surface area comparison, respectively.

Mutagenesis and fertility studies have not been conducted with ACTICLATE and ACTICLATE CAP. Mutagenesis studies with doxycycline demonstrated no potential to cause genetic toxicity in an in vitro point mutation study with mammalian cells or in an in vivo micronucleus assay in CD-1 mice. However, data from an in vitro mammalian chromosomal aberration assay conducted in CHO cells suggest that doxycycline is a weak clastogen. Oral administration of doxycycline to Sprague-Dawley rats showed adverse effects on fertility and reproduction including increased time for mating, reduced sperm motility, velocity and concentration as well as increased pre and post implantation loss. Reduced sperm velocity was seen at the lowest dosage tested, 50 mg/kg/day which is 2.5 times the maximum recommended daily adult dose of ACTICLATE and ACTICLATE CAP. Although doxycycline impairs the fertility of rats when administered at sufficient dosages, the effect of ACTICLATE and ACTICLATE CAP on human fertility is unknown.

13.2 Animal Toxicology and/or Pharmacology

Hyperpigmentation of the thyroid has been produced by members of the tetracycline-class in the following species: in rats by oxytetracycline, doxycycline, tetracycline PO4, and methacycline; in minipigs by doxycycline, minocycline, tetracycline PO4, and methacycline; in dogs by doxycycline and minocycline; in monkeys by minocycline.

Minocycline, tetracycline PO4, methacycline, doxycycline, tetracycline base, oxytetracycline HCl, and tetracycline HCl, were goitrogenic in rats fed a low iodine diet. This goitrogenic effect was accompanied by high radioactive iodine uptake. Administration of minocycline also produced a large goiter with high radioiodine uptake in rats fed a relatively high iodine diet.

Treatment of various animal species with this class of drugs has also resulted in the induction of thyroid hyperplasia in the following: in rats and dogs (minocycline); in chickens (chlortetracycline); and in rats and mice (oxytetracycline). Adrenal gland hyperplasia has been observed in goats and rats treated with oxytetracycline.

Results of animal studies indicate that tetracyclines cross the placenta and are found in fetal tissues.

15 REFERENCES

1. Friedman JM, Polifka JE. Teratogenic Effects of Drugs. A Resource for Clinicians (TERIS). Baltimore, MD: The Johns Hopkins University Press: 2000: 149-195. The TERIS (Teratogen Information System) is available at: http://www.micromedexsolutions.com/ (cited: 2016 Jan).
2. Cziezel AE and Rockenbauer M. Teratogenic study of doxycycline. Obstet Gynecol 1997; 89: 524-528.
3. Horne HW Jr. and Kundsin RB. The role of mycoplasma among 81 consecutive pregnancies: a prospective study. Int J Fertil 1980; 25: 315-317.
4. Drugs and Lactation Database (LactMed) [Internet]. Bethesda (MD): National Library of Medicine (US); [Last Revision Date 2015 March 10; cited 2016 Jan]. Doxycycline; LactMed Record Number: 100; [about 3 screens]. Available from: http://toxnet.nlm.nih.gov/newtoxnet/lactmed.htm
5. Clinical and Laboratory Standards Institute (CLSI). Performance Standards for Antimicrobial Susceptibility Testing; Twenty-seventh Informational Supplement. CLSI document M100S-S27. Clinical and Laboratory Standards Institute, 950 West Valley Road, Suite 2500, Wayne, Pennsylvania 19087, USA, 2017.
6. Clinical and Laboratory Standards Institute (CLSI). Methods for Dilution Antimicrobial Susceptibility Tests for Bacteria that Grow Aerobically; Approved Standard – Tenth Edition. CLSI document M07-A10, Clinical Laboratory Standards Institute, 950 West Valley Road, Suite 2500, Wayne, Pennsylvania 19087, USA, 2015.
7. Clinical and Laboratory Standards Institute (CLSI). Methods for Antimicrobial Dilution and Disk Susceptibility Testing of Infrequently Isolated or Fastidious Bacteria. Third Edition. CLSI Guideline M45, Clinical Laboratory Standards Institute, 950 West Valley Road, Suite 2500, Wayne, Pennsylvania 19087, USA, 2015.
8. Clinical and Laboratory Standards Institute (CLSI). Methods for Mycobacteria, Nocardiae, and Other Aerobic Actinomycetes; Approved Standard – Second Edition. CLSI document M24-A2, Clinical Laboratory Standards Institute, 950 West Valley Road, Suite 2500, Wayne, Pennsylvania 19087, USA, 2011.
9. Clinical and Laboratory Standards Institute (CLSI). Methods for Antimicrobial Susceptibility Testing for Human Mycoplasmas; Approved Guideline. CLSI document M43-A, Clinical Laboratory Standards Institute, 950 West Valley Road, Suite 2500, Wayne, Pennsylvania 19087, USA, 2011.
10. Clinical and Laboratory Standards Institute (CLSI). Performance Standards for Antimicrobial Disk Diffusion Susceptibility Tests; Approved Standard – Twelfth Edition. CLSI document M02-A12, Clinical Laboratory Standards Institute, 950 West Valley Road, Suite 2500, Wayne, Pennsylvania 19087, USA, 2015.
11. Clinical and Laboratory Standards Institute (CLSI). Methods for Antimicrobial Susceptibility Testing of Anaerobic Bacteria; Approved Standard – Eighth Edition. CLSI document M11-A8, Clinical Laboratory Standards Institute, 950 West Valley Road, Suite 2500, Wayne, Pennsylvania 19087, USA, 2012.

16 HOW SUPPLIED/STORAGE AND HANDLING

How Supplied

ACTICLATE (doxycycline hyclate) Tablets, 75 mg are round, convex, light-teal, film-coated, tablets with “75” debossed on one side of the tablet and “AQ101” debossed on the other. Each 75 mg tablet contains 86.6 mg of doxycycline hyclate equivalent to 75 mg of doxycycline.
Bottles of 60 tablets: NDC 16110-501-01

ACTICLATE (doxycycline hyclate) Tablets, 150 mg are oval-shaped, convex, mossy-green, film-coated tablets. Each side of the functionally scored tablet has two parallel score lines for splitting into 3 equal portions with “A” debossed on each portion of one side of the tablet, and no debossing on the other. Each 150 mg tablet contains 173.2 mg of doxycycline hyclate equivalent to 150 mg of doxycycline.
Bottles of 60 tablets: NDC 16110-502-01

ACTICLATE CAP (doxycycline hyclate) Capsules, 75 mg, have a navy blue opaque body and cap with the inscription “AQUA 101C75” in black. Each 75 mg capsule contains 86.6 mg of doxycycline hyclate equivalent to 75 mg of doxycycline.
Bottles of 60 capsules: NDC 16110-601-01

Storage
Store at 20° to 25°C (68° to 77°F) excursions permitted to 15° to 30°C (59° to 86°F) [See USP Controlled Room Temperature]. Protect from light and moisture. Dispense in a tight, light-resistant container as defined in the USP using a child-resistant closure.

17 PATIENT COUNSELING INFORMATION

Advise the patient to read the FDA-approved patient labeling (Instructions for Use).
Advise patients taking ACTICLATE and ACTICLATE CAP for malaria prophylaxis:

- that no present-day antimalarial agent, including doxycycline, guarantees protection against malaria.
- to avoid being bitten by mosquitoes by using personal protective measures that help avoid contact with mosquitoes, especially from dusk to dawn (for example, staying in well-screened areas, using mosquito nets, covering the body with clothing, and using an effective insect repellent).
- that doxycycline prophylaxis:
  - should begin 1 day to 2 days before travel to the malarious area,
  - should be continued daily while in the malarious area and after leaving the malarious area,
  - should be continued for 4 further weeks to avoid development of malaria after returning from an endemic area,
  - should not exceed 4 months.
  Advise all patients taking ACTICLATE and ACTICLATE CAP:
- that ACTICLATE Tablets (150 mg) can be broken into two-thirds or one-third at the scored lines to provide 100 mg or 50 mg strength doses, respectively.
- that they must swallow ACTICLATE CAP whole. They must not break, open, crush, dissolve or chew the capsule [see Dosage and Administration (2.2)].
- to avoid excessive sunlight or artificial ultraviolet light while receiving doxycycline and to discontinue therapy if phototoxicity (for example, skin eruptions, etc.) occurs. Sunscreen or sunblock should be considered [see Warnings and Precautions (5.3)].
- to drink fluids liberally along with ACTICLATE and ACTICLATE CAP to reduce the risk of esophageal irritation and ulceration [see Adverse Reactions (6)].
- that the absorption of tetracyclines is reduced when taken with foods, especially those that contain calcium [see Drug Interactions (7.3)]. However, the absorption of doxycycline is not markedly influenced by simultaneous ingestion of food or milk [see Clinical Pharmacology (12.3)].
- that if gastric irritation occurs, ACTICLATE and ACTICLATE CAP may be given with food or milk [see Clinical Pharmacology (12.3)].
- that the absorption of tetracyclines is reduced when taken with antacids containing aluminum, calcium or magnesium, bismuth subsalicylate, and iron-containing preparations [see Drug Interactions (7.3)].
- that the use of doxycycline might increase the incidence of vaginal candidiasis.

Advise patients that diarrhea is a common problem caused by antibacterial drugs which usually ends when the antibacterial is discontinued. Sometimes after starting treatment with antibacterial drugs, patients can develop watery and bloody stools (with or without stomach cramps and fever) even as late as two or more months after having taken the last dose of antibacterial. If this occurs, patients should contact their physician as soon as possible.

Counsel patients that antibacterial drugs including ACTICLATE and ACTICLATE CAP should only be used to treat bacterial infections. They do not treat viral infections (for example, the common cold). When ACTICLATE and ACTICLATE CAP are prescribed to treat a bacterial infection, patients should be told that although it is common to feel better early in the course of therapy, the medication should be taken exactly as directed. Skipping doses or not completing the full course of therapy may (1) decrease the effectiveness of the immediate treatment and (2) increase the likelihood that bacteria will develop resistance and will not be treatable by ACTICLATE and ACTICLATE CAP or other antibacterial drugs in the future.

Manufactured by Catalent Pharma Solutions, Winchester, KY 40391
For Aqua Pharmaceuticals, an Almirall Company Exton, PA 19341

AQUA PHARMACEUTICALS
an Almirall company

PATIENT INFORMATION

INSTRUCTIONS FOR USE

FDA-Approved Patient Labeling

Instructions for Use
ACTICLATE® (‘aktəˌklāt)
(doxycycline hyclate)
tablets
for oral use

Read this Instructions for Use before you start using ACTICLATE and each time you get a refill. There may be new information. This information does not take the place of talking to your healthcare provider about your medical condition or treatment.

Note:

- Your healthcare provider may need to change your dose of ACTICLATE during treatment as needed.
- ACTICLATE tablets can be taken whole or broken at scored lines.
- ACTICLATE tablets are marked with scored lines and may be broken at these scored lines to provide the following doses:

150 mg treatment (take the entire whole tablet)

100 mg treatment (take two-thirds of the tablet)

50 mg treatment (take one-third of the tablet)

How to break your ACTICLATE tablet:

- Hold the tablet between your thumb and index finger close to the scored line for your dose of ACTICLATE as shown above.
- Apply enough pressure to break the tablet at the scored line.
- Do not break the ACTICLATE tablet in any other way.

AQUA PHARMACEUTICALS
an Almirall company

Manufactured by Catalent Pharma Solutions, Winchester, KY 40391
For Aqua Pharmaceuticals, an Almirall Company Exton, PA 19341

This Instructions for Use has been approved by the U.S. Food and Drug Administration.
Revised: 10/2017
Rx only